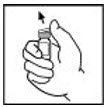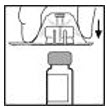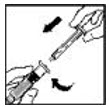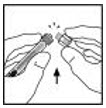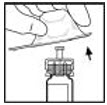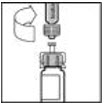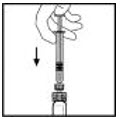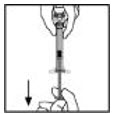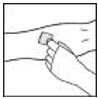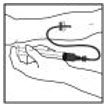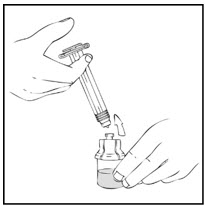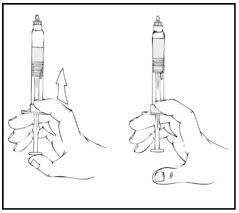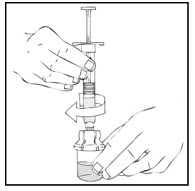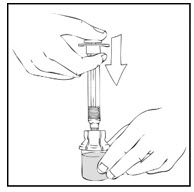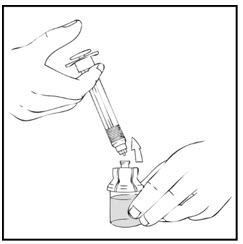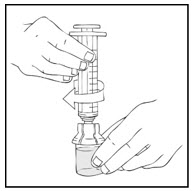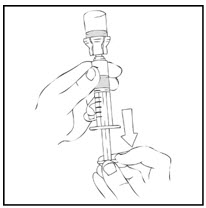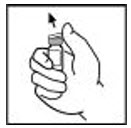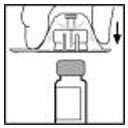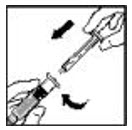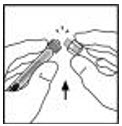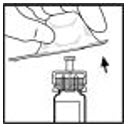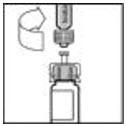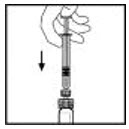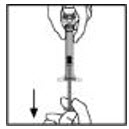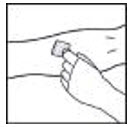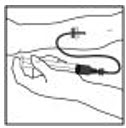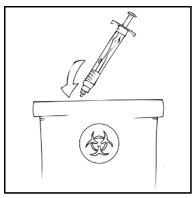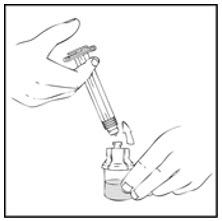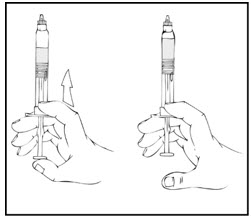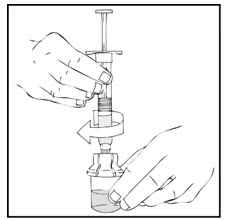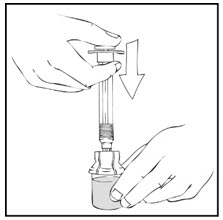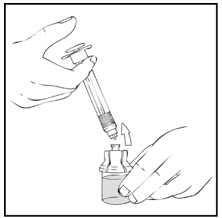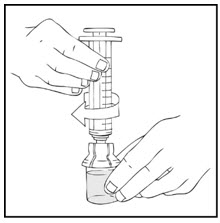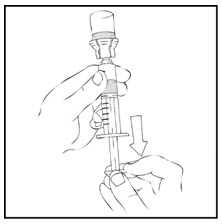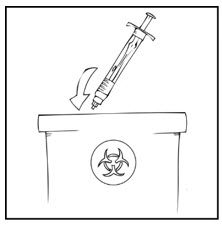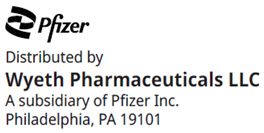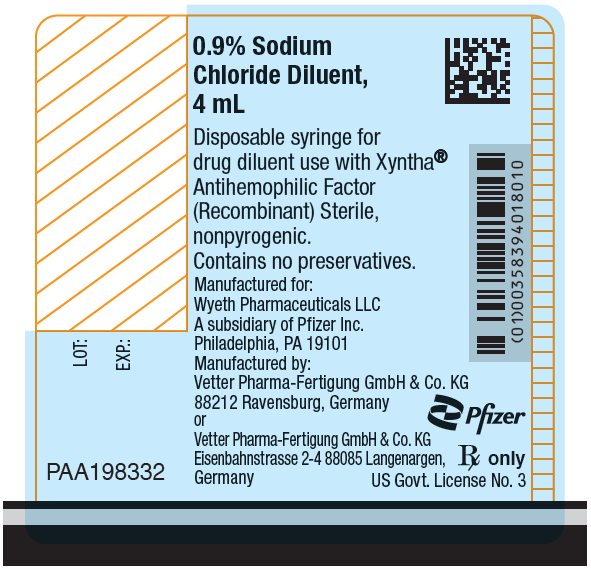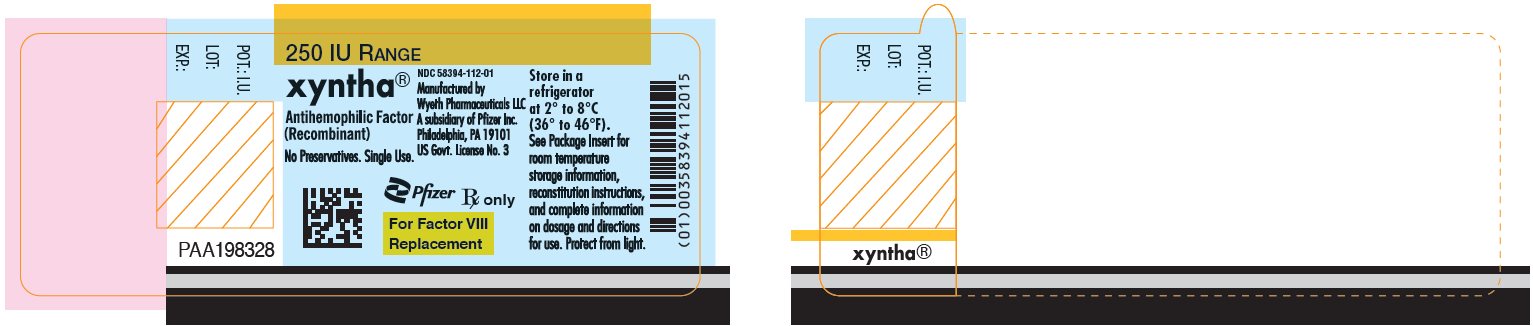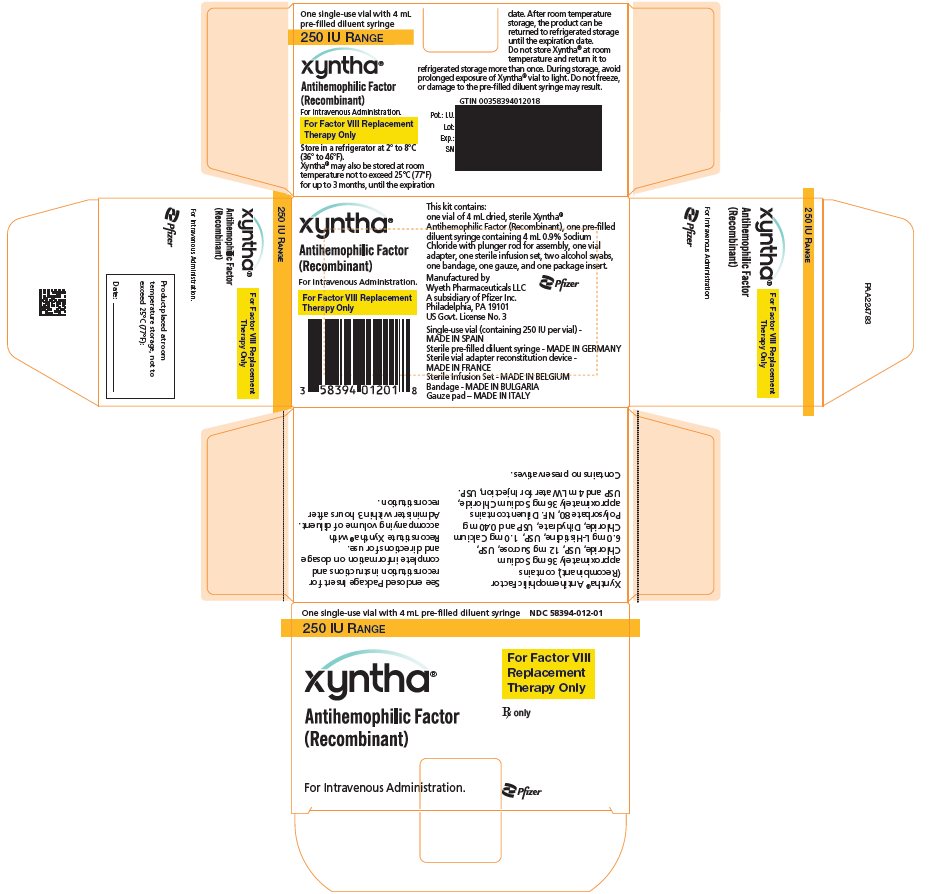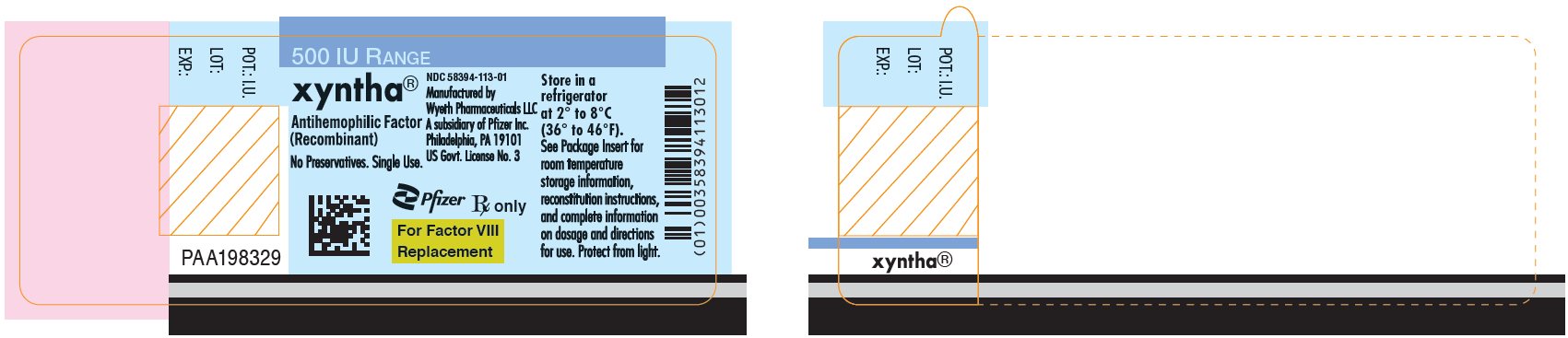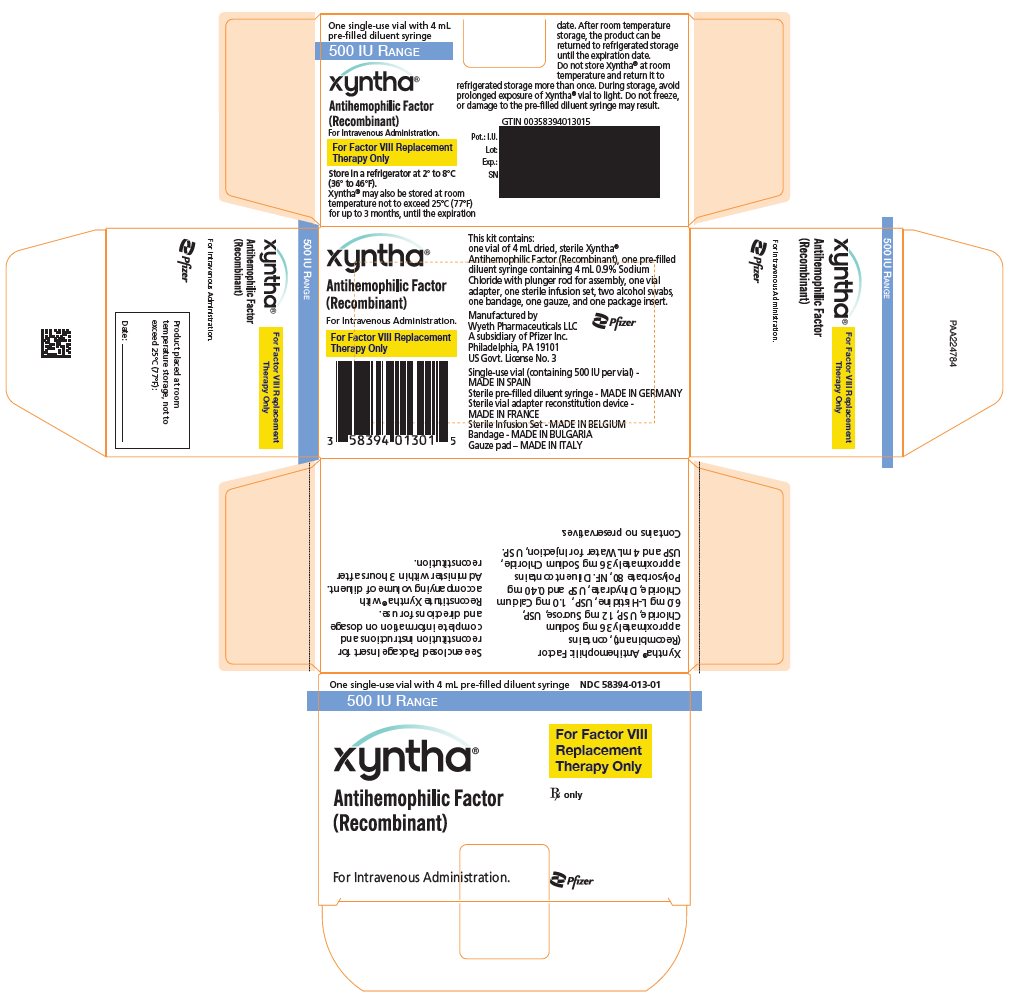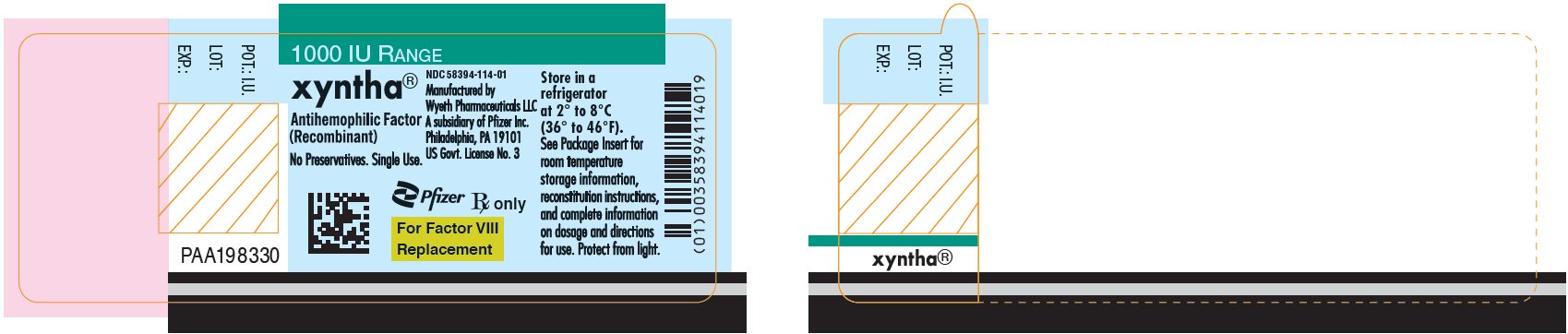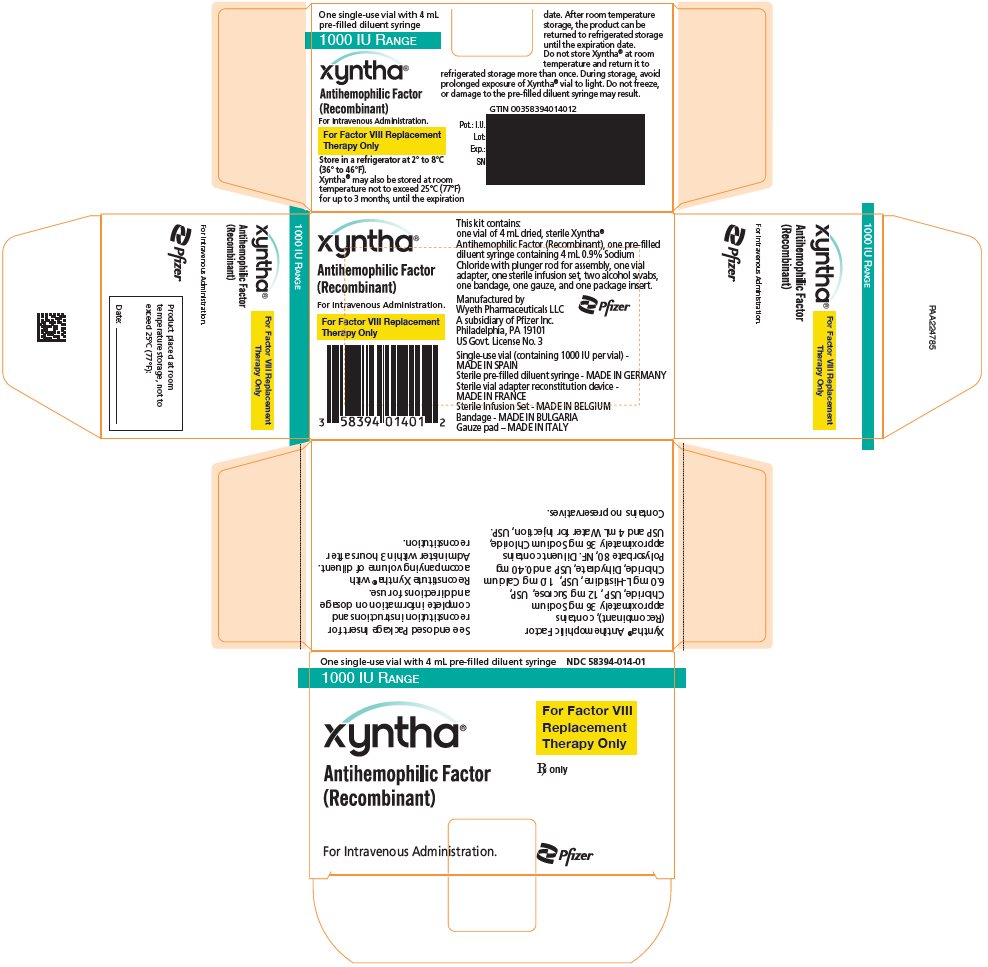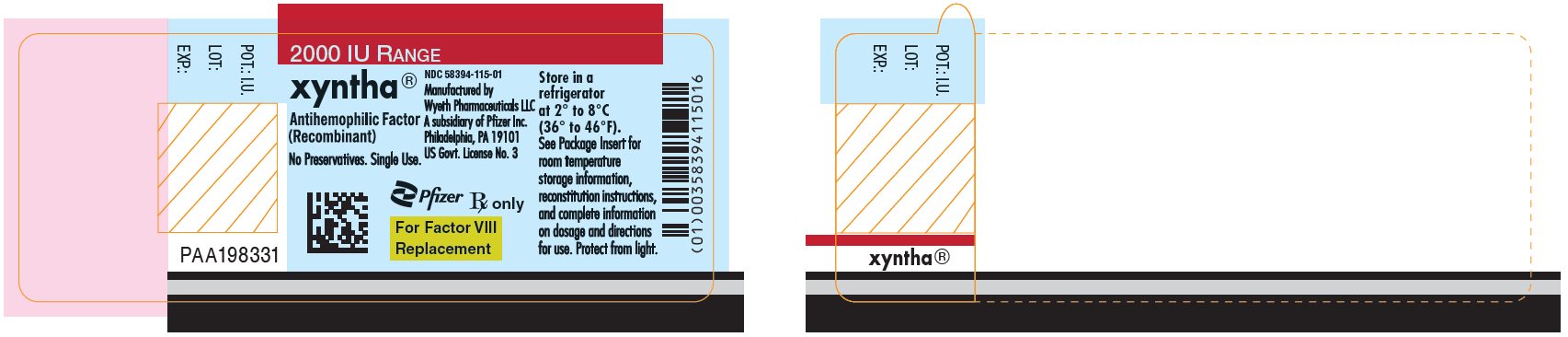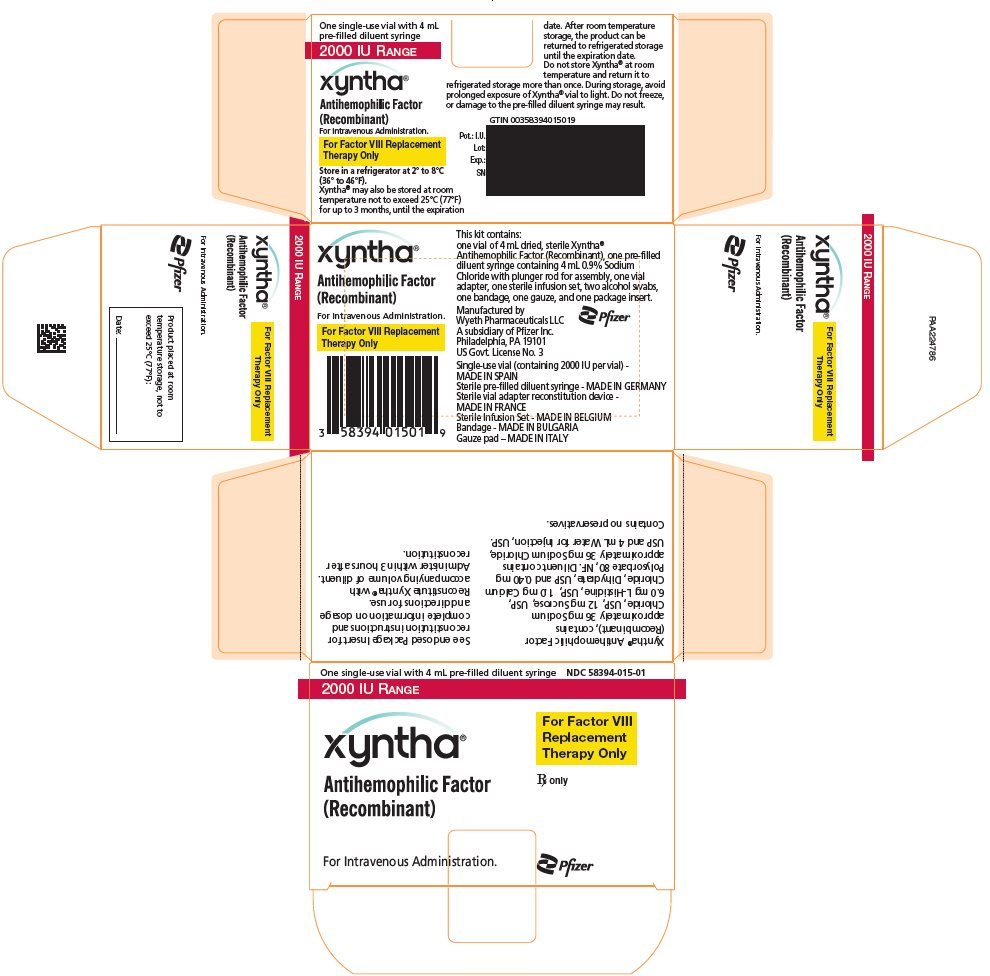 DRUG LABEL: Xyntha
NDC: 58394-012 | Form: KIT | Route: INTRAVENOUS
Manufacturer: Wyeth BioPharma Division of Wyeth Pharmaceuticals LLC
Category: other | Type: PLASMA DERIVATIVE
Date: 20250227

ACTIVE INGREDIENTS: MOROCTOCOG ALFA 250 [iU]/4 mL; ISOPROPYL ALCOHOL 70 mL/100 mL
INACTIVE INGREDIENTS: SODIUM CHLORIDE; SUCROSE; HISTIDINE; CALCIUM CHLORIDE; POLYSORBATE 80; SODIUM CHLORIDE 0.036 mg/4 mL; WATER 4 mL/4 mL; WATER

HIGHLIGHTS OF PRESCRIBING INFORMATION

These highlights do not include all the information needed to use XYNTHA safely and effectively. See full prescribing information for XYNTHA.
XYNTHA® (antihemophilic factor [recombinant]) lyophilized powder for solution, for intravenous injection
Initial U.S. Approval: 2008

1 INDICATIONS AND USAGE

- XYNTHA is a recombinant antihemophilic factor indicated in adults and children with hemophilia A for on-demand treatment and control of bleeding episodes, for perioperative management, and for routine prophylaxis to reduce the frequency of bleeding episodes. (1)
- XYNTHA is not indicated in patients with von Willebrand's disease. (1)

2 DOSAGE AND ADMINISTRATION

For intravenous use after reconstitution only (2)

- The required dose is determined using the following formula:
  Required units = body weight (kg) × desired factor VIII rise (IU/dL or % of normal) × 0.5 (IU/kg per IU/dL), where IU = International Unit. (2.1)

Routine prophylaxis (2.1)

- Adults and adolescents (≥12 years): The recommended starting regimen is 30 IU/kg of XYNTHA administered 3 times weekly.
- Children (<12 years): The recommended starting regimen is 25 IU/kg of XYNTHA administered every other day. More frequent or higher doses may be required in children <12 years of age to account for the higher clearance in this age group.
- Adjust the dosing regimen (dose or frequency) based on the patient's clinical response.
- Frequency of XYNTHA administration is determined by the type of bleeding episode and the recommendation of the treating physician. (2.1, 2.2)

3 DOSAGE FORMS AND STRENGTHS

XYNTHA is available as lyophilized powder in single-use vials containing nominally 250, 500, 1000, or 2000 IU. (3)

4 CONTRAINDICATIONS

Do not use in patients who have manifested life-threatening immediate hypersensitivity reactions, including anaphylaxis, to the product or its components, including hamster proteins. (4)

5 WARNINGS AND PRECAUTIONS

- Anaphylaxis and severe hypersensitivity reactions are possible. Patients may develop hypersensitivity to hamster protein, which is present in trace amounts in XYNTHA. Should such reactions occur, discontinue treatment with the product and administer appropriate treatment. (5.1)
- Development of neutralizing antibodies has been reported in patients using XYNTHA. If expected plasma factor VIII activity levels are not attained, or if bleeding is not controlled with an appropriate dose, perform an assay that measures factor VIII inhibitor concentration. (5.2, 5.3, 6.2)

6 ADVERSE REACTIONS

- The most common adverse reactions (≥10%) with XYNTHA in adult and pediatric previously treated patients (PTPs) were headache, arthralgia, pyrexia, and cough. (6)
- Across all studies, 4 subjects developed factor VIII inhibitors (2.4%). (6.2)

To report SUSPECTED ADVERSE REACTIONS, contact Wyeth Pharmaceuticals LLC. at 1-800-438-1985 or FDA at 1-800-FDA-1088 or www.fda.gov/medwatch

8 USE IN SPECIFIC POPULATIONS

Pediatrics: Half-lives are shorter, volumes of distribution are larger, and recovery is lower after XYNTHA administration in children. Higher or more frequent dosing may be needed. (8.4)

FULL PRESCRIBING INFORMATION

1 INDICATIONS AND USAGE

XYNTHA, Antihemophilic Factor (Recombinant), is indicated for use in adults and children with hemophilia A (congenital factor VIII deficiency) for:

- On-demand treatment and control of bleeding episodes
- Perioperative management
- Routine prophylaxis to reduce the frequency of bleeding episodes

XYNTHA does not contain von Willebrand factor, and therefore is not indicated in patients with von Willebrand's disease.

2 DOSAGE AND ADMINISTRATION

For intravenous use after reconstitution only.

2.1 Dose

- Dosage and duration of treatment depend on the severity of the factor VIII deficiency, the location and extent of bleeding, and the patient's clinical condition. Titrate the administered doses to the patient's clinical response.
- One International Unit (IU) of factor VIII activity corresponds approximately to the quantity of factor VIII in one milliliter of normal human plasma. The calculation of the required dosage of factor VIII is based upon the empirical finding that, on average, 1 IU of factor VIII per kg body weight raises the plasma factor VIII activity by approximately 2 IU/dL.^2

The expected in vivo peak increase in factor VIII level expressed as IU/dL (or % of normal) can be estimated using the following formulas:

Dosage (International Units) = body weight (kg) × desired factor VIII rise (IU/dL or % of normal) × 0.5 (IU/kg per IU/dL)

or

IU/dL (or % of normal) = Total Dose (IU)/body weight (kg) × 2 [IU/dL]/[IU/kg]

On-demand treatment and Control of Bleeding Episodes

A guide for dosing XYNTHA for on-demand treatment and control of bleeding episodes is provided in Table 1. Maintain the plasma factor VIII activity at or above the levels (in % of normal or in IU/dL) outlined in Table 1 for the indicated period.

Table 1: Dosing for On-demand Treatment and Control of Bleeding Episodes
Type of Bleeding Episode | Factor VIII Level Required (IU/dL or % of normal) | Frequency of Doses (hours) | Duration of Therapy
Minor
Early hemarthrosis, minor muscle or oral bleeds. | 20–40 | 12–24 | At least 1 day, depending upon the severity of the bleeding episode.
Moderate
Bleeding into muscles. Mild head trauma. Bleeding into the oral cavity. | 30–60 | 12–24 | 3–4 days or until adequate local hemostasis is achieved.
Major
Gastrointestinal bleeding. Intracranial, intra-abdominal, or intrathoracic bleeding. Fractures. | 60–100 | 8–24 | Until bleeding is resolved.

Perioperative Management

A guide for dosing XYNTHA during surgery (perioperative management) is provided in Table 2. Maintain the plasma factor VIII activity level at or above the level (in % of normal or in IU/dL) outlined in Table 2 for the indicated period. Monitor the replacement therapy by means of plasma factor VIII activity.

Table 2: Dosing for Perioperative Management
Type of Surgery | Factor VIII Level Required (IU/dL or % of normal) | Frequency of Doses (hours) | Duration of Therapy (days)
Minor
Minor operations, including tooth extraction. | 30–60 | 12–24 | 3–4 days or until adequate local hemostasis is achieved. For tooth extraction, a single infusion plus oral antifibrinolytic therapy within 1 hour may be sufficient.
Major
Major operations. | 60–100 | 8–24 | Until threat is resolved, or in the case of surgery, until adequate local hemostasis and wound healing are achieved.

Routine Prophylaxis

- Adults and adolescents (≥12 years): The recommended starting regimen is 30 IU/kg of XYNTHA administered 3 times weekly.
- Children (<12 years): The recommended starting regimen is 25 IU/kg of XYNTHA administered every other day. More frequent or higher doses may be required in children <12 years of age to account for the higher clearance in this age group [see Clinical Pharmacology (12.3)].
- Adjust the dosing regimen (dose or frequency) based on the patient's clinical response.

2.2 Preparation and Reconstitution

Preparation

1. Always wash hands before performing the following procedures.
2. Use aseptic technique during the reconstitution procedures.
3. Use all components in the reconstitution and administration of this product as soon as possible after opening their sterile containers to minimize unnecessary exposure to the atmosphere.

Note:

- If the patient uses more than one vial of XYNTHA per infusion, reconstitute each vial according to the following instructions. Remove the diluent syringe, leaving the vial adapter in place. Use a separate 10 milliliter or larger luer lock syringe (not included in this kit) to draw back the reconstituted contents of each vial. Do not detach the diluent syringe or the large luer lock syringe until ready to attach the large luer lock syringe to the next vial adapter.
- If the patient uses one vial of XYNTHA with one XYNTHA SOLOFUSE® for the infusion, reconstitute the vial and the syringe according to the instructions for each respective product kit. Use a separate 10 milliliter or larger luer lock syringe (not included in this kit) to draw back the reconstituted contents of the vial and the syringe. [see Dosage and Administration (2.4)]

Reconstitution

1. Allow the XYNTHA vial and the prefilled diluent syringe to reach room temperature.
2. Remove the plastic flip-top cap from the XYNTHA vial to expose the central portions of the rubber stopper.
3. Wipe the top of the vial with the alcohol swab provided, or use another antiseptic solution, and allow to dry. After cleaning, do not touch the rubber stopper or allow it to touch any surface.
4. Peel back the cover from the clear plastic vial adapter package. Do not remove the adapter from the package.
5. Place the XYNTHA vial on a flat surface. While holding the adapter package, place the vial adapter over the XYNTHA vial and press down firmly on the package until the adapter spike penetrates the vial stopper.
6. Grasp the plunger rod as shown in the diagram. Avoid contact with the shaft of the plunger rod. Attach the threaded end of the plunger rod to the diluent syringe plunger by pushing and turning firmly.
7. Break off the tamper-resistant plastic tip cap from the diluent syringe by snapping the perforation of the cap. Do not touch the inside of the cap or the syringe tip. The diluent syringe may need to be recapped (if not administering reconstituted XYNTHA immediately), so place the cap on its top on a clean surface in a spot where it would be least likely to become environmentally contaminated.
8. Lift the package away from the adapter and discard the package.
9. Place the XYNTHA vial, with the adapter attached, on a flat surface. Connect the diluent syringe to the vial adapter by inserting the tip into the adapter opening while firmly pushing and turning the syringe clockwise until secured.
10. Slowly depress the plunger rod to inject all the diluent into the XYNTHA vial.
11. Without removing the syringe, gently swirl the contents of the XYNTHA vial until the powder is dissolved.
  Note: The final solution should be inspected visually for particulate matter before administration. The solution should be clear to slightly opalescent and colorless. If it is not, discard the solution and use a new kit.
12. Invert the XYNTHA vial and slowly draw the solution into the syringe.
13. Detach the syringe from the vial adapter by gently pulling and turning the syringe counterclockwise. Discard the empty XYNTHA vial with the adapter attached.

Note:

- If the solution is not used immediately, carefully replace the syringe cap. Do not touch the syringe tip or the inside of the cap.
- Store the reconstituted solution at room temperature prior to administration, but use within 3 hours after reconstitution.
- XYNTHA, when reconstituted, contains polysorbate 80, which is known to increase the rate of di-(2-ethylhexyl) phthalate (DEHP) extraction from polyvinyl chloride (PVC). This should be considered during the preparation and administration of XYNTHA, including storage time elapsed in a PVC container following reconstitution. The tubing of the infusion set included with this kit does not contain DEHP.

2.3 Administration

For intravenous infusion after reconstitution only.

Inspect the final XYNTHA solution visually for particulate matter and discoloration prior to administration, whenever solution and container permit. The solution should be clear to slightly opalescent and colorless. If it is not, discard the solution and use a new kit.

Use the tubing and the prefilled diluent syringe provided in this kit or a single sterile disposable plastic syringe. Do not administer XYNTHA in the same tubing or container with other medicinal products.

1. Attach the syringe to the luer end of the infusion set tubing provided.
2. Apply a tourniquet and prepare the injection site by wiping the skin well with an alcohol swab provided in the kit.
3. Remove the protective needle cover and perform venipuncture. Insert the needle on the infusion set tubing into the vein, and remove the tourniquet. Verify proper needle placement.
4. Inject the reconstituted XYNTHA product intravenously over several minutes. The rate of administration should be determined by the patient's comfort level.
5. After infusing XYNTHA, remove and discard the infusion set. The amount of drug product left in the infusion set will not affect treatment.
  Note: Dispose of all unused solution, the empty vial(s), and other used medical supplies in an appropriate container.

2.4 Use of a XYNTHA Vial Kit with a XYNTHA SOLOFUSE Kit

These instructions are for the use of only one XYNTHA Vial Kit with one XYNTHA SOLOFUSE Kit.

1. Reconstitute the XYNTHA vial using the instructions described in Preparation and Reconstitution [see Dosage and Administration (2.2)].
2. Detach the empty diluent syringe from the vial adapter by gently turning and pulling the syringe counterclockwise, leaving the contents in the XYNTHA vial with the vial adapter in place.
3. Reconstitute the XYNTHA SOLOFUSE using the instructions included with the product kit, remembering to remove most, but not all, of the air from the drug product chamber.
4. After removing the protective blue vented cap, connect the XYNTHA SOLOFUSE to the vial adapter by inserting the tip into the adapter opening while firmly pushing and turning the syringe clockwise until secured.
5. Slowly depress the plunger rod of the XYNTHA SOLOFUSE until the contents empty into the XYNTHA vial. The plunger rod may move back slightly after release.
6. Detach and discard the empty XYNTHA SOLOFUSE from the vial adapter.
  Note: If the syringe turns without detaching from the vial adapter, grasp the white collar and turn.
7. Connect a sterile 10 milliliter or larger luer lock syringe to the vial adapter. Inject some air into the vial to make withdrawing the vial contents easier.
8. Invert the vial and slowly draw the solution into the large luer lock syringe.
9. Detach the syringe from the vial adapter by gently turning and pulling the syringe counterclockwise. Discard the vial with the adapter attached.
10. Attach the infusion set to the large luer lock syringe as directed [see Dosage and Administration (2.3)].

3 DOSAGE FORMS AND STRENGTHS

XYNTHA is available as a white to off-white lyophilized powder in the following nominal dosages:

- 250 International Units
- 500 International Units
- 1000 International Units
- 2000 International Units

Each XYNTHA vial has the actual recombinant factor VIII (rFVIII) potency in International Units stated on the label.

4 CONTRAINDICATIONS

XYNTHA is contraindicated in patients who have manifested life-threatening immediate hypersensitivity reactions, including anaphylaxis, to the product or its components, including hamster proteins.

5 WARNINGS AND PRECAUTIONS

5.1 Hypersensitivity Reactions

Allergic-type hypersensitivity reactions, including anaphylaxis, are possible with XYNTHA. Inform patients of the early signs or symptoms of hypersensitivity reactions (including hives [rash with itching], generalized urticaria, chest tightness, wheezing, and hypotension) and anaphylaxis. Discontinue XYNTHA if hypersensitivity symptoms occur and administer appropriate emergency treatment.

XYNTHA contains trace amounts of hamster proteins. Patients treated with this product may develop hypersensitivity to these non-human mammalian proteins.

5.2 Neutralizing Antibodies

Inhibitors have been reported following administration of XYNTHA. Monitor patients for the development of factor VIII inhibitors by appropriate clinical observations and laboratory tests. If expected factor VIII activity plasma levels are not attained, or if bleeding is not controlled with an appropriate dose, perform an assay that measures factor VIII inhibitor concentration to determine if a factor VIII inhibitor is present [see Warnings and Precautions (5.3)].^4,5,6,7,8,9,10,11,12

5.3 Monitoring Laboratory Tests

- Use individual factor VIII values for recovery and, if clinically indicated, other pharmacokinetic characteristics to guide dosing and administration.
- Monitor plasma factor VIII activity levels by the one-stage clotting assay to confirm that adequate factor VIII levels have been achieved and are maintained, when clinically indicated [see Dosage and Administration (2)].
- Monitor for development of factor VIII inhibitors. Perform assay to determine if factor VIII inhibitor is present when expected factor VIII activity plasma levels are not attained, or when bleeding is not controlled with the expected dose of XYNTHA. Use Bethesda Units (BU) to titer inhibitors.

6 ADVERSE REACTIONS

The most common adverse reactions (≥10%) with XYNTHA in adult and pediatric previously treated patients (PTPs) were headache, arthralgia, pyrexia, and cough.

6.1 Clinical Trials Experience

Because clinical trials are conducted under widely varying conditions, adverse reaction rates observed in the clinical trials of a drug cannot be directly compared to rates in the clinical trials of another drug and may not reflect the rates observed in clinical practice.

XYNTHA was evaluated in five completed clinical studies (N=178), comprising four studies with adult and pediatric PTPs.

The safety and efficacy of XYNTHA was evaluated in two completed pivotal studies. In the first study (n=94), safety and efficacy were examined in PTPs with severe to moderately severe hemophilia A (factor VIII activity in plasma [FVIII:C] ≤2%) who received XYNTHA for routine prophylaxis and on-demand treatment. Ninety-four subjects received at least one dose of XYNTHA, resulting in a total of 6,775 infusions [see Clinical Studies (14)]. The second study (n=30) examined the use of XYNTHA for surgical prophylaxis in PTPs with severe to moderately severe hemophilia A (FVIII:C ≤2%) who required elective major surgery and were expected to receive XYNTHA replacement therapy for at least 6 days post-surgery. All subjects received at least one dose of XYNTHA, resulting in 1,161 infusions. One subject received XYNTHA for a pre-surgery pharmacokinetic assessment only and did not undergo surgery [see Clinical Studies (14)].

Across all studies, safety was evaluated in 72 pediatric PTPs <17 years of age (46 subjects <6 years of age (4 subjects were 0 to <2 years of age), 4 subjects 6 to <12 years of age, and 22 adolescents, 12 to <17 years of age). A total of 13,109 infusions of XYNTHA were administered with a median dose per infusion of 28 IU/kg (min-max: 6–108 IU/kg).

Across all studies, the most common adverse reactions (≥10%) with XYNTHA in adult and pediatric PTPs were headache (24%), arthralgia (23%), pyrexia (23%), and cough (12%). Other adverse reactions reported in ≥5% of subjects were: diarrhea (8%), vomiting (8%), and asthenia (6%).

6.2 Immunogenicity

There is a potential for immunogenicity with therapeutic proteins. The development of factor VIII inhibitors with XYNTHA was evaluated in 167 adult and pediatric PTPs with at least 50 exposure days (EDs). Laboratory-based assessments for FVIII inhibitor (partial Nijmegen modification of the Bethesda inhibitor assay) were conducted in the clinical studies. The criterion for a positive FVIII result test result was ≥0.6 BU/mL. Across all studies, 4 subjects developed factor VIII inhibitors (2.4%).

The completed clinical studies for XYNTHA examined 178 subjects (30 for surgical prophylaxis) who had previously been treated with factor VIII (PTPs). In the first safety and efficacy study, factor VIII inhibitors were detected in two of 89 subjects (2.2%) who completed ≥50 EDs. In a Bayesian statistical analysis, results from this study were used to update PTP results from a prior supporting study using XYNTHA manufactured at the initial facility (with one de novo and two recurrent inhibitors observed in 110 subjects) and the experience with predecessor product (with one inhibitor observed in 113 subjects). The Bayesian analysis indicated that the population inhibitor rate for XYNTHA, an estimate of the 95% upper limit of the true inhibitor rate, was 4.17%.

None of the PTPs developed anti-CHO (Chinese hamster ovary) or anti-TN8.2 antibodies. One PTP developed anti-FVIII antibodies; but, this subject did not develop an inhibitor.

In the surgery study, one low titer persistent inhibitor and one transient false-positive inhibitor were reported. In this study, one surgical subject developed anti-CHO cell antibodies with no associated allergic reaction. One subject developed anti-FVIII antibodies; but, this subject did not develop an inhibitor.

Across all studies, immunogenicity was evaluated in 64 pediatric PTPs <17 years of age with at least 50 EDs (43 children <6 years of age, 4 subjects 6 to <12 years of age, and 17 adolescents, 12 to <17 years of age). Of these, 2 pediatric subjects developed an inhibitor.

The detection of antibody formation is highly dependent on the sensitivity and specificity of the assay. Additionally, the observed incidence of antibody, including neutralizing antibody, positivity in an assay may be influenced by several factors, including assay methodology, sample handling, timing of sample collection, concomitant medications, and underlying disease. For these reasons, comparisons of the incidence of antibodies to XYNTHA with the incidence of antibodies to other products may be misleading.

6.3 Postmarketing Experience

Because these reactions are reported voluntarily from a population of uncertain size, it is not always possible to reliably estimate their frequency or establish a causal relationship to drug exposure.

The following postmarketing adverse reaction has been reported for XYNTHA:

Inadequate therapeutic response

8 USE IN SPECIFIC POPULATIONS

8.1 Pregnancy

Risk Summary

It is not known whether XYNTHA can cause fetal harm when administered to a pregnant woman or can affect reproduction capacity. Animal reproduction studies have not been conducted with XYNTHA.

There is no information available on the effect of factor VIII replacement therapy on labor and delivery. XYNTHA should be used only if clinically indicated.

In the U.S. general population, the estimated background risk of major birth defects and miscarriage in clinically recognized pregnancies is 2–4% and 15–20%, respectively.

8.2 Lactation

Risk Summary

There is no information regarding the presence of XYNTHA in human milk, the effect on the breastfed infant, or the effects on milk production. The developmental and health benefits of breastfeeding should be considered along with the mother's clinical need for XYNTHA and any potential adverse effects on the breastfed child from XYNTHA or from the underlying maternal condition.

8.4 Pediatric Use

Safety and efficacy with XYNTHA were evaluated in clinical studies in 68 pediatric subjects <17 years of age (18 subjects aged 12 to <17 years, 50 subjects aged ≤12 years). There were no apparent differences in the efficacy and safety in pediatric subjects as compared to adults [see Adverse Reactions (6.1) and Clinical Studies (14)].

In comparison to the pharmacokinetic parameters reported in adults, children have shorter half-lives, larger volumes of distribution and lower recovery of factor VIII after XYNTHA administration. The clearance (based on per kg body weight) is approximately 40% higher in children. Higher or more frequent doses may be required to account for the observed differences in pharmacokinetic parameters [see Clinical Pharmacology (12.3)].

8.5 Geriatric Use

Clinical studies of XYNTHA did not include sufficient numbers of subjects aged 65 and over to determine whether they respond differently from younger subjects. Other reported clinical experience has not identified differences in responses between the elderly and younger patients. In general, dose selection for an elderly patient should be cautious, usually starting at the low end of the dosing range, reflecting the greater frequency of decreased hepatic, renal, or cardiac function and of concomitant disease or other drug therapy.

11 DESCRIPTION

The active ingredient in XYNTHA, Antihemophilic Factor (Recombinant), is a recombinant antihemophilic factor (rAHF), also called coagulation factor VIII, which is produced by recombinant DNA technology. It is secreted by a genetically engineered Chinese hamster ovary (CHO) cell line. The cell line is grown in a chemically defined cell culture medium that contains recombinant insulin, but does not contain any materials derived from human or animal sources.

The rAHF in XYNTHA is a purified glycoprotein, with an approximate molecular mass of 170 kDa consisting of 1,438 amino acids, which does not contain the B-domain.^13 The amino acid sequence of the rAHF is comparable to the 90 + 80 kDa form of human coagulation factor VIII.

The purification process uses a series of chromatography steps, one of which is based on affinity chromatography using a patented synthetic peptide affinity ligand.^14 The process also includes a solvent-detergent viral inactivation step and a virus-retaining nanofiltration step.

The potency expressed in International Units (IU) is determined using the chromogenic assay of the European Pharmacopoeia. The Wyeth manufacturing reference standard for potency has been calibrated against the World Health Organization (WHO) International Standard for factor VIII activity using the one-stage clotting assay. The specific activity of XYNTHA is 5,500 to 9,900 IU per milligram of protein.

XYNTHA is formulated as a sterile, nonpyrogenic, no preservative, lyophilized powder preparation for intravenous injection. Each single-use vial contains nominally 250, 500, 1000, or 2000 IU of XYNTHA. Upon reconstitution, the product is a clear to slightly opalescent, colorless solution that contains sodium chloride, sucrose, L-histidine, calcium chloride, and polysorbate 80.

12 CLINICAL PHARMACOLOGY

12.1 Mechanism of Action

XYNTHA temporarily replaces the missing clotting factor VIII that is needed for effective hemostasis.

12.2 Pharmacodynamics

The activated partial thromboplastin time (aPTT) is prolonged in patients with hemophilia. Determination of aPTT is a conventional in vitro assay for biological activity of factor VIII. Treatment with XYNTHA normalizes the aPTT over the effective dosing period.

12.3 Pharmacokinetics

The pharmacokinetic parameters of XYNTHA in 30 PTPs 12 to 60 years old, who received a single infusion of 50 IU/kg XYNTHA are summarized in Table 3.

In addition, 25 of the same subjects later received a single infusion of 50 IU/kg of XYNTHA for a 6-month follow-up pharmacokinetic study. The parameters were comparable between baseline and 6 months, indicating no time-dependent changes in the pharmacokinetics of XYNTHA.

In a separate study, 8 of 30 subjects at least 12 years old with hemophilia A undergoing elective major surgery received a single 50 IU/kg infusion of XYNTHA. The pharmacokinetic parameters in these subjects are also summarized in Table 3.

Table 3: Mean ± SD XYNTHA Pharmacokinetic Parameters in Previously Treated Patients with Hemophilia A after Single 50 IU/kg Dose
Parameter | Initial Visit (n = 30) | Month 6 (n = 25) | Pre-surgery (n=8)
Cmax (IU/mL) | 1.08 ± 0.22 | 1.24 ± 0.42 | 1.08 ± 0.24
AUC∞ (IU∙hr/mL) | 13.5 ± 5.6 | 15.0 ± 7.5 | 16.0 ± 5.2
t1/2 (hr) | 11.2 ± 5.0 | 11.8 ± 6.2 [One subject was excluded from the calculation due to lack of a well-defined terminal phase.] | 16.7 ± 5.4
CL (mL/hr/kg) | 4.51 ± 2.23 | 4.04 ± 1.87 | 3.48 ± 1.25
Vss (mL/kg) | 66.1 ± 33.0 | 67.4 ± 32.6 | 69.0 ± 20.1
Recovery (IU/dL per IU/kg) | 2.15 ± 0.44 | 2.47 ± 0.84 | 2.17 ± 0.47
Abbreviations: AUC∞ = area under the plasma concentration-time curve from zero to infinity; Cmax = peak concentration; t1/2 = plasma elimination half-life; CL = clearance; n = number of subjects; SD = standard deviation; Vss = volume of distribution at steady-state.

Table 4 shows the pharmacokinetic parameters of nine children; four aged 14 or 15 years of age, who are also included in the summary for the adults above, along with five children aged 3.7–5.8 years after single 50 IU/kg doses of XYNTHA. Compared to adults, the half-life of XYNTHA is shorter in children and the clearance (based on per kg body weight) is approximately 40% higher in children.

Table 4: Mean ± SD XYNTHA Pharmacokinetic Parameters in Previously Treated Pediatric Patients with Hemophilia A after Single 50 IU/kg Dose
Parameter | Young Children (n = 5) | Adolescents (n = 4)
Age (min-max, yr) | 3.7–5.8 | 14–15
Cmax (IU/mL) | 0.78 ± 0.34 | 0.97 ± 0.21
AUC∞ (IU∙hr/mL) | 12.2 ± 6.50 | 8.5 ± 4.0
t1/2 (hr) | 8.3 ± 2.7 | 6.9 ± 2.4
CL (mL/hr/kg) | 6.29 ± 4.87 | 6.62 ± 2.16
Vss (mL/kg) | 66.9 ± 55.6 | 67.1 ± 13.6
Recovery (IU/dL per IU/kg) | 1.52 ± 0.69 | 1.95 ± 0.41
Abbreviations: AUC∞ = area under the plasma concentration-time curve from zero to infinity; Cmax = peak concentration; t1/2 = plasma elimination half-life; CL = clearance; n = number of subjects; SD = standard deviation; Vss = volume of distribution at steady-state.

13 NONCLINICAL TOXICOLOGY

13.1 Carcinogenesis, Mutagenesis, Impairment of Fertility

No studies have been conducted with XYNTHA to assess its mutagenic or carcinogenic potential. XYNTHA has been shown to be comparable to the predecessor product with respect to its biochemical and physicochemical properties, as well as its nonclinical in vivo pharmacology and toxicology. By inference, predecessor product and XYNTHA would be expected to have equivalent mutagenic and carcinogenic potential. The predecessor product has been shown to be nongenotoxic in the mouse micronucleus assay. No studies have been conducted in animals to assess impairment of fertility or fetal development.

13.2 Animal Toxicology and/or Pharmacology

Preclinical studies evaluating XYNTHA in hemophilia A dogs without inhibitors demonstrated safe and effective restoration of hemostasis. XYNTHA demonstrated a toxicological profile that was similar to the toxicological profile observed with the predecessor product. Toxicity associated with XYNTHA was primarily associated with anti-FVIII neutralizing antibody generation first detectable at 15 days of repeat dosing in high (approximately 735 IU/kg/day) level-dosed, non-human primates.

14 CLINICAL STUDIES

Three completed multicenter, open-label studies support the analysis of safety and efficacy of XYNTHA in on-demand treatment and control of bleeding episodes and perioperative management, and routine prophylaxis in PTPs with hemophilia A. These completed clinical studies for XYNTHA examined 174 PTP subjects, 94 from the first study, and 50 from a second study, for on-demand treatment and routine prophylaxis and 30 from a third study for surgical prophylaxis. Subjects with severe to moderately severe hemophilia A (FVIII:C ≤2%) and no history of FVIII inhibitors were eligible for the trials.

On-demand Treatment and Control of Bleeding Episodes

On-demand treatment in adolescents and adults

Ninety-four (94) subjects, 12 years of age and older received XYNTHA in a routine prophylaxis treatment regimen with on-demand treatment administered as clinically indicated. All 94 subjects were treated with at least one dose and all are included in the intent-to-treat (ITT) population. Eighty-nine (89) subjects accrued ≥50 EDs. Median age for the 94 treated subjects was 24 years (mean 28 and min-max: 12–60 years).

Of these 94 subjects, 30 evaluable subjects participated in a randomized crossover pharmacokinetics substudy. Twenty-five (25/30) of these subjects with FVIII:C ≤1% completed both the first (PK1) and the second (PK2) pharmacokinetic assessments [see Clinical Pharmacology (12.3)].^16

Fifty-three subjects (53/94) received XYNTHA on-demand treatment for a total of 187 bleeding episodes. Seven of these bleeding episodes occurred in subjects prior to switching to a prophylaxis treatment regimen. One hundred ten of 180 bleeds (110/180 or 61%) occurred ≤48 hours after the last dose and 39% (70/180 bleeds) occurred >48 hours after the last dose. The majority of bleeds reported to occur ≤48 hours after the last prophylaxis dose were traumatic (64/110 bleeds or 58%). Forty-two bleeds (42/70 or 60%) reported to occur >48 hours after the last prophylaxis dose were spontaneous. The on-demand treatment dosing regimen was determined by the investigator. The median dose for on-demand treatment was 31 IU/kg (min-max: 6–74 IU/kg) and the median exposure per subject was 3 days (min-max: 1–26).

The majority of bleeding episodes (173/187 or 93%) resolved with 1 or 2 infusions (Table 5). One hundred thirty-two of 187 bleeding episodes (132/187 or 71%) treated with XYNTHA were rated excellent or good in their response to initial treatment, 45 (24%) were rated moderate. Five (3%) were rated no response, and 5 (3%) were not rated.

Table 5: Summary of Response to Infusions to Treat New Bleeding Episode by Number of Infusions Needed for Resolution
Response to 1st Infusion | Number of Infusions (%) 1 | Number of Infusions (%) 2 | Number of Infusions (%) 3 | Number of Infusions (%) 4 | Number of Infusions (%) >4 | Total Number of Bleeds
Excellent [Excellent: Definite pain relief and/or improvement in signs of bleeding starting within 8 hours after an infusion, with no additional infusion administered.] | 42 (95.5) | 2 (4.5) | 0 (0.0) | 0 (0.0) | 0 (0.0) | 44
Good [Good: Definite pain relief and/or improvement in signs of bleeding starting within 8 hours after an infusion, with at least one additional infusion administered for complete resolution of the bleeding episode.] | 69 (78.4) | 16 (18.2) | 3 (3.4) | 0 (0.0) | 0 (0.0) | 88
Moderate [Moderate: Probable or slight improvement starting after 8 hours following the infusion, with at least one additional infusion administered for complete resolution of the bleeding episode.] | 24 (53.3) | 16 (35.6) | 2 (4.4) | 0 (0.0) | 3 (6.7) | 45
No Response [No Response: No improvement at all between infusions or during the 24 hour interval following an infusion, or condition worsens.] | 0 (0.0) | 0 (0.0) | 2 (40.0) | 2 (40.0) | 1 (20.0) | 5
Not Assessed | 4 (80.0) | 0 (0.0) | 0 (0.0) | 1 (20.0) | 0 (0.0) | 5 [Includes one infusion with commercial FVIII that occurred before routine prophylaxis began.]
Total | 139 (74.3) | 34 (18.2) | 7 (3.7) | 3 (1.6) | 4 (2.1) | 187

Of the 94 subjects described above, in the first completed open-label safety and efficacy study of XYNTHA, 18 were adolescent subjects 12 to <17 years of age with severe to moderately severe hemophilia A (FVIII:C ≤2%). Ten (10) of these adolescent subjects, received XYNTHA for the on-demand treatment of 66 bleeding episodes, with the majority of the bleeding episodes (63/66 or 95%) resolving with 1 or 2 infusions. The response to infusion was rated on a pre-specified 4 point hemostatic efficacy scale. Thirty-eight (38) of 66 bleeding episodes (58%) were rated excellent or good in their response to initial treatment, 24 (36%) were rated as moderate, and 4 (6%) were not rated. The median dose per on demand infusion was 47 IU/kg (min-max: 24–74).

On-demand treatment in children

Additional data for 50 subjects are available from a second safety and efficacy study of XYNTHA in children (≤12 years of age) with severe to moderately severe hemophilia A (FVIII:C ≤2%). Of the 50 subjects, 38 subjects received XYNTHA for on-demand and follow-up treatment of 562 bleeding episodes with the majority of the bleeding episodes (518/562 or 92%) resolving with 1 or 2 infusions. Of 559 bleeding episodes treated with XYNTHA with response assessments to the first infusion, 526 (94%) were rated excellent or good in their response to initial treatment and 27 (5%) were rated as moderate. The median dose per on-demand infusion was 28 IU/kg (min-max: 10–92).

Perioperative Management

In a study (n=30) for surgical prophylaxis in subjects with hemophilia A, XYNTHA was administered to 25 efficacy-evaluable PTPs undergoing major surgical procedures (11 total knee replacements, 1 hip replacement, 5 synovectomies, 1 left ulnar nerve transposition release, 1 ventral hernia repair/scar revision, 1 knee arthroscopy, 1 revision and debridement of the knee after a total knee replacement, 1 hip arthroplasty revision, 1 stapes replacement, 1 ankle arthrodesis, and 1 pseudotumor excision).^17

The results of the hemostatic efficacy ratings for these subjects are presented in Table 6. Investigator's ratings of efficacy at the end of surgery and at the end of the initial postoperative period were excellent or good for all assessments. Intraoperative blood loss was reported as "normal" or "absent" for all subjects. Thirteen of the subjects (13/25 or 52%) had blood loss in the postoperative period. The postoperative blood loss was rated as "normal" for ten of these cases while three cases were rated "abnormal" (1 due to hemorrhage following surgical trauma to the epigastric artery, 1 due to an 800 mL blood loss after hip replacement surgery, and 1 after an elbow synovectomy where the blood loss could not be measured by the investigator).

Table 6: Summary of Hemostatic Efficacy
Time of Hemostatic Efficacy Assessment | Excellent [Excellent: Achieved hemostasis comparable to that expected after similar surgery in a patient without hemophilia.] | Good [Good: Prolonged time to hemostasis, with somewhat increased bleeding compared with that expected after similar surgery in a patient without hemophilia.] | Number of subjects
End of surgery | 18 (72%) | 7 (28%) | 25
End of initial postoperative period [End of initial postoperative period is date of discharge or postoperative Day 6, whichever occurs later.] | 23 (92%) | 2 (8%) | 25

Routine Prophylaxis

One hundred and two (102) subjects (94 subjects ≥12 years of age and 8 subjects <12 years of age) received XYNTHA for routine prophylaxis, for comparison of annualized bleeding rate (ABR) to on-demand treatment alone as a part of 2 completed studies. XYNTHA was administered for routine prophylaxis at a dose of 25 ± 5 IU/kg every other day (in subjects <12 years of age) or 30 ± 5 IU/kg administered 3 times weekly (in subjects 12 years of age or older), with provisions for dose escalation based on pre-specified criteria (over a 4-week period, 2 spontaneous bleeds into a major joint and/or target joint, or 3 or more spontaneous bleeding episodes in any location). Among these 102 subjects, 7 dose escalations were prescribed for 6 subjects.

In subjects ≥12 years, 42 subjects (42/94 or 45%) reported no bleeding while on routine prophylaxis. The mean±SD total ABR during routine prophylaxis was 4.0±6.64 with median (min-max) of 1.9 (0.0–44.2). The mean ABR for subjects during routine prophylaxis was 88% lower than the mean ABR for subjects during on-demand treatment (Table 7).

In subjects <12 years, 4 subjects (4/8 or 50%) reported no bleeding while on routine prophylaxis. The mean±SD total ABR during routine prophylaxis was 1.5±2.2 with median (min-max) of 0.6 (0.0–6.2). The mean ABR for subjects during routine prophylaxis was 97% lower than the mean ABR for subjects during on-demand treatment (Table 7).

Table 7: Summary of Annualized Bleeding Rate During Routine Prophylaxis Treatment with XYNTHA
Age Category (years) | Number of Subjects | % Reduction from OD | Treated Total Routine Prophylaxis ABR Mean ± SD Median (Min-Max) | Treated Spontaneous Routine Prophylaxis ABR Mean ± SD Median (Min-Max) | Treated Traumatic Routine Prophylaxis ABR Mean ± SD Median (Min-Max)
0 to <12 | 8 | 97% | 1.5 ± 2.20 | 0.6 ± 1.31 | 0.9 ± 1.30
 |  |  | 0.6 (0.0–6.2) | 0.0 (0.0–3.7) | 0.0 (0.0–3.2)
≥12 | 94 [The treated total ABR mean ± SD during prophylaxis for the 93 subjects aged ≥12 years (outlier removed), was 3.6 ± 5.18 with median (min-max) of 1.9 (0.0–23.3). The spontaneous treated ABR mean ± SD was 1.6 ± 2.87 with median (min-max) of 0.0 (0.0–13.7). The traumatic ABR mean ± SD was 1.9 ± 3.99 with median (min-max) of 0.0 (0.0–23.3).] | 88% | 4.0 ± 6.64 | 2.0 ± 4.25 | 2.0 ± 4.10
 |  |  | 1.9 (0.0–44.2) | 0.0 (0.0–32.1) | 0.0 (0.0–23.3)
12 to <17 | 18 [The treated total ABR mean ± SD during prophylaxis for the 17 adolescents (outlier removed), was 5.2 ± 6.90 with median (min-max) of 2.0 (0.0–21.4). The spontaneous ABR mean ± SD was 1.6 ± 2.94 with median (min-max) of 0.0 (0.0–11.6). The traumatic ABR mean ± SD was 3.5 ± 5.77 with median (min-max) of 1.9 (0.0–19.6).] | 84% | 7.3 ± 11.37 | 3.3 ± 7.73 | 4.0 ± 5.94
 |  |  | 3.0 (0.0–44.2) | 0.0 (0.0–32.1) | 1.9 (0.0–19.6)
≥17 | 76 | 89% | 3.2 ± 4.70 | 1.6 ± 2.88 | 1.6 ± 3.42
 |  |  | 1.9 (0.0–23.3) | 0.0 (0.0–13.7) | 0.0 (0.0–23.3)
OD = on demand; ABR = annualized bleeding rate; SD = standard deviation, Min = minimum, Max = maximum.

15 REFERENCES

1. Nilsson IM, Berntorp EE and Freiburghaus C. Treatment of patients with factor VIII and IX inhibitors. Thromb Haemost. 1993;70(1):56–59.
2. Hoyer LW. Hemophilia A. N Engl J Med. 1994;330:38–47.
3. Juhlin F. Stability and Compatibility of Reconstituted Recombinant Factor VIII SQ, 250 IU/ml, in a System for Continuous Infusion. Pharmacia Document 9610224, 1996.
4. Ehrenforth S, Kreuz W, Scharrer I, et al. Incidence of development of factor VIII and factor IX inhibitors in hemophiliacs. Lancet. 1992;339:594–598.
5. Lusher J, Arkin S, Abildgaard CF, Schwartz RS, the Kogenate PUP Study Group. Recombinant factor VIII for the treatment of previously untreated patients with hemophilia A. N Engl J Med. 1993;328:453–459.
6. Bray GL, Gomperts ED, Courter S, et al. A multicenter study of recombinant factor VIII (Recombinate): safety, efficacy, and inhibitor risk in previously untreated patients with hemophilia A. Blood. 1994;83(9):2428–2435.
7. Kessler C, Sachse K. Factor VIII:C inhibitor associated with monoclonal-antibody purified FVIII concentrate. Lancet. 1990;335:1403.
8. Schwartz RS, Abildgaard CF, Aledort LM, et al. Human recombinant DNA-derived antihemophilic factor (factor VIII) in the treatment of hemophilia A. N Engl J Med. 1990;323:1800–1805.
9. White GC II, Courter S, Bray GL, et al. A multicenter study of recombinant factor VIII (Recombinate™) in previously treated patients with hemophilia A. Thromb Haemost. 1997;77(4):660–667.
10. Gruppo R, Chen H, Schroth P, et al. Safety and immunogenicity of recombinant factor VIII (Recombinate™) in previously untreated patients: A 7.3 year update. Haemophilia. 1998;4:228 (Abstract No. 291, XXIII Congress of the WFH, The Hague).
11. Scharrer I, Bray GL, Neutzling O. Incidence of inhibitors in haemophilia A patients - a review of recent studies of recombinant and plasma-derived factor VIII concentrates. Haemophilia. 1999;5:145–154.
12. Abshire TC, Brackmann HH, Scharrer I, et al. Sucrose formulated recombinant human antihemophilic Factor VIII is safe and efficacious for treatment of hemophilia A in home therapy: Results of a multicenter, international, clinical investigation. Thromb Haemost. 2000;83(6):811–816.
13. Sandberg H, Almstedt A, Brandt J, Castro VM, Gray E, Holmquist L, et al. Structural and Functional Characterization of B-Domain Deleted Recombinant Factor VIII. Sem Hematol. 2001;38 (Suppl. 4):4–12.
14. Kelley BD, Tannatt M, Magnusson R, Hagelberg S. Development and Validation of an Affinity Chromatography Step Using a Peptide Ligand for cGMP Production of Factor VIII. Biotechnol Bioeng. 2004;87(3):400–412.
15. Mann KG and Ziedens KB. Overview of Hemostasis. In: Lee CA, Berntorp EE and Hoots WK, eds. Textbook of Hemophilia. USA, Blackwell Publishing; 2005:1–4.
16. Recht M, Nemes L, Matysiak M et al. Clinical Evaluation of Moroctocog Alfa (AF-CC), a New Generation of B-Domain Deleted Recombinant Factor VIII (BDDrFVIII) for Treatment of Haemophilia A: Demonstration of Safety, Efficacy and Pharmacokinetic Equivalence to Full-length Recombinant Factor VIII. Haemophilia 2009; 1–12.
17. Windyga J, Rusen L, Gruppo R, et al. BDDrFVIII (Moroctocog alfa [AF-CC]) for surgical haemostasis in patients with haemophilia A: results of a pivotal study. Haemophilia. 2010 Sep 1;16(5):731–9.

16 HOW SUPPLIED/STORAGE AND HANDLING

How Supplied

Each XYNTHA Vial Kit contains: one prefilled diluent syringe containing 4 mL 0.9% Sodium Chloride with plunger rod for assembly, one vial adapter, one sterile infusion set, two alcohol swabs, one bandage, one gauze pad, and one package insert. The drug product, diluents for injection and the rest of components included within the XYNTHA 250, 500, 1000, or 2000 International Units kit are free from natural rubber and natural rubber latex.

XYNTHA is supplied in kits that include single-use vials containing nominally 250, 500, 1000, or 2000 International Units lyophilized powder per vial:

XYNTHA Vial Kit
Nominal Strength | Fill Size Color Indicator | Vial Kit NDC #
250 International Units | Yellow | 58394-012-01
500 International Units | Blue | 58394-013-01
1000 International Units | Green | 58394-014-01
2000 International Units | Red | 58394-015-01

Actual factor VIII activity in International Units is stated on the label of each XYNTHA vial.

Storage and Handling

- Store XYNTHA under refrigeration at a temperature of 2° to 8°C (36° to 46°F) for up to 36 months from the date of manufacture until the expiration date stated on the label.
- Within the expiration date, XYNTHA also may be stored at room temperature not to exceed 25°C (77°F) for up to 3 months.
- After room temperature storage, XYNTHA can be returned to the refrigerator until the expiration date. Do not store XYNTHA at room temperature and return it to the refrigerator more than once.
- Clearly record the starting date at room temperature storage in the space provided on the outer carton. At the end of the 3-month period, immediately use, discard, or return the product to refrigerated storage. The diluent syringe may be stored at 2° to 25°C (36° to 77°F).
- Do not use XYNTHA after the expiration date.
- Do not freeze. (Freezing may damage the prefilled diluent syringe.)
- During storage, avoid prolonged exposure of XYNTHA vial to light.
- Store the reconstituted solution at room temperature prior to administration. Administer XYNTHA within 3 hours after reconstitution.

17 PATIENT COUNSELING INFORMATION

Advise patients to:

- read the FDA-approved patient labeling (Patient Information and Instructions for Use).
- report any adverse reactions or problems that concern them when taking XYNTHA to their healthcare provider.
- discontinue use of the product, call their healthcare provider, and go to the emergency department if any allergic-type hypersensitivity reactions occur. Inform patients of the early signs of hypersensitivity reactions (including hives [rash with itching]), generalized urticaria, tightness of the chest, wheezing, hypotension) and anaphylaxis.
- contact their healthcare provider if they experience a lack of a clinical response to factor VIII replacement therapy, as this may be a manifestation of an inhibitor.
- notify their healthcare provider if they become pregnant or intend to become pregnant during therapy, or if they are breastfeeding.

For Medical Information about XYNTHA, please visit www.pfizermedinfo.com or call 1-800-438-1985.

FDA-Approved Patient Labeling

Patient Information

XYNTHA® /ZIN-tha/
[Antihemophilic Factor (Recombinant)]

Please read this patient information carefully before using XYNTHA and each time you get a refill. There may be new information. This leaflet does not take the place of talking with your healthcare provider about your medical problems or your treatment.

What is XYNTHA?

XYNTHA is an injectable medicine that is used to help control and reduce bleeding in people with hemophilia A. Hemophilia A is also called classic hemophilia. Your healthcare provider may give you XYNTHA when you have surgery.

XYNTHA is not used to treat von Willebrand's disease.

What should I tell my healthcare provider before using XYNTHA?

Tell your healthcare provider about all of your medical conditions, including if you:

- have any allergies, including allergies to hamsters.
- are pregnant or planning to become pregnant. It is not known if XYNTHA may harm your unborn baby.
- are breastfeeding. It is not known if XYNTHA passes into your milk and if it can harm your baby.

Tell your healthcare provider about all of the medicines you take, including all prescription and non-prescription medicines, such as over-the-counter medicines, supplements, or herbal remedies.

How should I infuse XYNTHA?

Step-by-step instructions for infusing with XYNTHA are provided at the end of this leaflet.

The steps listed below are general guidelines for using XYNTHA. Always follow any specific instructions from your healthcare provider. If you are unsure of the procedures, please call your healthcare provider before using.

Call your healthcare provider right away if bleeding is not controlled after using XYNTHA.

Call your healthcare provider right away if you take more than the dose you should take.

Talk to your healthcare provider before traveling. Plan to bring enough XYNTHA for your treatment during this time.

What are the possible side effects of XYNTHA?

Call your healthcare provider or go to the emergency department right away if you have any of the following symptoms because these may be signs of a serious allergic reaction:

- wheezing
- difficulty breathing
- chest tightness
- turning blue (look at lips and gums)
- fast heartbeat
- swelling of the face
- faintness
- rash
- hives

Common side effects of XYNTHA are

- headache
- joint pain
- fever
- cough
- vomiting
- diarrhea
- weakness

Your body can make antibodies against XYNTHA (called "inhibitors") that may stop XYNTHA from working properly. Your healthcare provider may need to take blood tests from time to time to monitor for inhibitors.

Talk to your healthcare provider about any side effect that bothers you or that does not go away. You may report side effects to FDA at 1-800-FDA-1088.

How should I store XYNTHA?

Store XYNTHA in the refrigerator at 36° to 46°F (2° to 8°C). Store the diluent syringe at 36° to 77°F (2° to 25°C).

Do not freeze.

Protect from light.

XYNTHA can last at room temperature (below 77°F) for up to 3 months. If you store XYNTHA at room temperature, carefully write down the date you put XYNTHA at room temperature, so you will know when to either put it back in the refrigerator, use it immediately, or throw it away. There is a space on the carton for you to write the date.

If stored at room temperature, XYNTHA can be returned one time to the refrigerator until the expiration date. Do not store at room temperature and return it to the refrigerator more than once. Throw away any unused XYNTHA after the expiration date.

Infuse XYNTHA within 3 hours of reconstitution. You can keep the reconstituted solution at room temperature before infusion for up to 3 hours. If you have not used it in 3 hours, throw it away.

Do not use reconstituted XYNTHA if it is not clear to slightly opalescent and colorless.

Dispose of all materials, whether reconstituted or not, in an appropriate medical waste container.

What else should I know about XYNTHA?

Medicines are sometimes prescribed for purposes other than those listed here. Talk to your healthcare provider if you have any concerns. You can ask your healthcare provider for information about XYNTHA that was written for healthcare professionals.

Do not share XYNTHA with other people, even if they have the same symptoms that you have.

Instructions for Use

XYNTHA® /ZIN-tha/
[Antihemophilic Factor (Recombinant)]

XYNTHA is supplied as a lyophilized powder. Before you can infuse it (intravenous injection), you must reconstitute the powder by mixing it with the liquid diluent supplied. The liquid diluent is 0.9% sodium chloride.

Reconstitute and infuse XYNTHA using the infusion set, diluent, syringe, and adapter provided in this kit. Please follow the directions below for the proper use of this product.

PREPARATION AND RECONSTITUTION OF XYNTHA

Preparation

1. Always wash your hands before doing the following steps.
2. Keep everything clean and germ-free while you are reconstituting XYNTHA.
3. Once the vials are open, finish reconstituting XYNTHA as soon as possible. This will help to keep them germ-free.
4. For additional instructions on the use of a XYNTHA Vial Kit and a XYNTHA SOLOFUSE kit, see detailed information provided after the INFUSION OF XYNTHA section.

Reconstitution

Note: If you use more than one vial of XYNTHA for each infusion, reconstitute each vial according to steps 1 through 11.

1. Let the XYNTHA vial and the prefilled diluent syringe reach room temperature.
2. Remove the plastic flip-top cap from the XYNTHA vial to show the center part of the rubber stopper.
3. Wipe the top of the vial with the alcohol swab provided, or use another antiseptic solution, and allow to dry. After cleaning, do not touch the rubber stopper with your hand or allow it to touch any surface.
4. Peel back the cover from the clear plastic vial adapter package. Do not remove the adapter from the package.
5. Place the XYNTHA vial on a flat surface. While holding the adapter in the package, place the vial adapter over the XYNTHA vial. Press down firmly on the package until the adapter snaps into place on top of the vial, with the adapter spike going into the vial stopper.
6. Grasp the plunger rod as shown in the picture below. Do not touch the shaft of the plunger rod. Attach the threaded end of the plunger rod to the diluent syringe plunger by pushing and turning firmly.
7. Break off the tamper-resistant, plastic tip cap from the diluent syringe by snapping the perforation of the cap. Do not touch the inside of the cap or the syringe tip. The diluent syringe may need to be recapped (if reconstituted XYNTHA is not used immediately), so place the cap on its top on a clean surface in a spot where it will stay clean.
8. Lift the package cover away from the adapter and throw the package away.
9. Place the XYNTHA vial on a flat surface. Connect the diluent syringe to the vial adapter by inserting the tip of the syringe into the adapter opening while firmly pushing and turning the syringe clockwise until the connection is secured.
10. Slowly push the plunger rod to inject all the diluent into the XYNTHA vial.
11. With the syringe still connected to the adapter, gently swirl the contents of the vial until the powder is dissolved.
  Look carefully at the final solution. The solution should be clear to slightly opalescent and colorless. If it is not, throw away the solution and use a new kit.
12. Make sure the syringe plunger rod is still fully pressed down, then turn over the XYNTHA vial. Slowly pull the solution into the syringe. Turn the syringe upward again and remove any air bubbles by gently tapping the syringe with your finger and slowly pushing air out of the syringe.
  If you reconstituted more than one vial of XYNTHA, remove the diluent syringe from the vial adapter and leave the vial adapter attached to the XYNTHA vial. Quickly attach a separate large luer lock syringe and pull the reconstituted solution as instructed above. Repeat this procedure with each vial in turn. Do not detach the diluent syringe or the large luer lock syringe until you are ready to attach the large luer lock syringe to the next vial adapter.
13. Remove the syringe from the vial adapter by gently pulling and turning the syringe counterclockwise. Throw away the empty XYNTHA vial with the adapter attached.

Note:

- If you are not using the solution right away, carefully replace the syringe cap. Do not touch the syringe tip or the inside of the cap.
- Infuse XYNTHA solution within 3 hours after reconstitution. The reconstituted solution may be kept at room temperature for up to 3 hours prior to infusion. If you have not used it in 3 hours, throw it away.

INFUSION OF XYNTHA

Your healthcare provider will teach you how to infuse XYNTHA yourself. Once you learn how to do this, you can follow the instructions in this insert.

Before XYNTHA can be infused, you must reconstitute it as instructed above in the PREPARATION AND RECONSTITUTION OF XYNTHA section.

After reconstitution, be sure to look carefully at the XYNTHA solution. The solution should be clear to slightly opalescent and colorless. If it is not, throw away the solution and use a new kit.

Use the infusion set included in the kit to infuse XYNTHA. Do not infuse XYNTHA in the same tubing or container with other medicines.

1. Attach the syringe to the luer end of the provided infusion set tubing.
2. Apply a tourniquet and prepare the injection site by wiping the skin well with an alcohol swab provided in the kit.
3. Remove the protective needle cover and insert the butterfly needle of the infusion set tubing into your vein as instructed by your healthcare provider. Remove the tourniquet. Verify proper needle placement.
4. Infuse the reconstituted XYNTHA product over several minutes. Your comfort level should determine the rate of infusion.
5. After infusing XYNTHA, remove the infusion set and throw it away. The amount of liquid left in the infusion set will not affect your treatment.

Note:

- Dispose of all unused solution, the empty vial(s), and other used medical supplies in an appropriate container.
- It is a good idea to record the lot number from the XYNTHA vial label every time you use XYNTHA. You can use the peel-off label found on the vial to record the lot number.

ADDITIONAL INSTRUCTIONS

XYNTHA is also supplied in kits that have both the XYNTHA powder and the diluent within single-use prefilled dual-chamber syringes, called XYNTHA SOLOFUSE.

If you use one XYNTHA vial and one of XYNTHA SOLOFUSE for the infusion, reconstitute the XYNTHA vial and the XYNTHA SOLOFUSE according to the specific directions for that respective product kit. Use a separate 10 milliliter or larger luer lock syringe (not included in this kit) to draw back the reconstituted contents of the XYNTHA vial and XYNTHA SOLOFUSE.

Use of a XYNTHA Vial Kit with a XYNTHA SOLOFUSE Kit

These instructions are for the use of only one XYNTHA vial kit and one XYNTHA SOLOFUSE Kit. For further information, please contact your healthcare provider or call the Medical Information Department at Wyeth Pharmaceuticals, 1-800-438-1985.

1. Reconstitute the XYNTHA vial using the instructions described in PREPARATION AND RECONSTITUTION OF XYNTHA section. Detach the empty diluent syringe from the vial adapter by gently turning and pulling the syringe counterclockwise, leaving the contents in the XYNTHA vial with the vial adapter in place.
2. Reconstitute the XYNTHA SOLOFUSE using the instructions included with the kit, remembering to remove most, but not all, of the air from the syringe.
3. After removing the protective blue vented cap, connect the XYNTHA SOLOFUSE to the vial adapter by inserting the tip into the adapter opening while firmly pushing and turning the syringe clockwise until secured.
4. Slowly depress the plunger rod of the XYNTHA SOLOFUSE until the contents empty into the XYNTHA vial. The plunger rod may move back slightly after release.
5. Detach the empty XYNTHA SOLOFUSE from the vial adapter and throw it away.
  If the syringe turns without detaching from the vial adapter, grasp the white collar and turn.
6. Connect a sterile 10 milliliter or larger luer lock syringe to the vial adapter. You may want to inject some air into the XYNTHA vial to make withdrawing the vial contents easier.
7. Invert the XYNTHA vial and slowly draw the solution into the large luer lock syringe.
8. Detach the large luer lock syringe from the vial adapter by gently turning and pulling the syringe counterclockwise. Throw away the empty XYNTHA vial with the adapter attached.
9. Attach the infusion set to the large luer lock syringe as directed in the INFUSION OF XYNTHA section.

Note: Dispose of all unused solution and other used medical supplies in an appropriate container.

This product's labeling may have been updated. For the most recent prescribing information, please visit www.pfizer.com.

License no: 3
LAB-0516-9.0

PRINCIPAL DISPLAY PANEL - 4 mL Syringe Label

0.9% Sodium
Chloride Diluent,
4 mL

Disposable syringe for
drug diluent use with Xyntha®
Antihemophilic Factor
(Recombinant) Sterile,
nonpyrogenic.
Contains no preservatives.

Manufactured for:
Wyeth Pharmaceuticals LLC
A subsidiary of Pfizer Inc
Philadelphia, PA 19101
Manufactured by:
Vetter Pharma-Fertigung GmbH & Co. KG
88212 Ravensburg, Germany
or
Vetter Pharma-Fertigung GmbH & Co. KG
Eisenbahnstrasse 2-4 88085 Langenargen,
Germany

Pfizer

Rx only

US Govt. License No. 3

LOT:

EXP:

PAA198332

PRINCIPAL DISPLAY PANEL - 250 IU Vial Label

250 IU RANGE

xyntha®
Antihemophilic Factor
(Recombinant)

No Preservatives. Single Use.

NDC 58394-112-01

Manufactured by
Wyeth Pharmaceuticals LLC
A subsidiary of Pfizer Inc.
Philadelphia, PA 19101
US Govt. License No. 3

Pfizer

Rx only

For Factor VIII
Replacement

PRINCIPAL DISPLAY PANEL - Kit Carton - 250 IU

One single-use vial with 4 mL pre-filled diluent syringe
NDC 58394-012-01

250 IU RANGE

xyntha®

Antihemophilic Factor
(Recombinant)

For Intravenous Administration.

For Factor VIII
Replacement
Therapy Only

Rx only

Pfizer

PRINCIPAL DISPLAY PANEL - 500 IU Vial Label

500 IU RANGE

xyntha®
Antihemophilic Factor
(Recombinant)

No Preservatives. Single Use.

NDC 58394-113-01

Manufactured by
Wyeth Pharmaceuticals LLC
A subsidiary of Pfizer Inc.
Philadelphia, PA 19101
US Govt. License No. 3

Pfizer

Rx only

For Factor VIII
Replacement

PRINCIPAL DISPLAY PANEL - Kit Carton - 500 IU

One single-use vial with 4 mL pre-filled diluent syringe
NDC 58394-013-01

500 IU RANGE

xyntha®

Antihemophilic Factor
(Recombinant)

For Intravenous Administration.

For Factor VIII
Replacement
Therapy Only

Rx only

Pfizer

PRINCIPAL DISPLAY PANEL - 1000 IU Vial Label

1000 IU RANGE

xyntha®
Antihemophilic Factor
(Recombinant)

No Preservatives. Single Use.

NDC 58394-114-01

Manufactured by
Wyeth Pharmaceuticals LLC
A subsidiary of Pfizer Inc.
Philadelphia, PA 19101
US Govt. License No. 3

Pfizer

Rx only

For Factor VIII
Replacement

PRINCIPAL DISPLAY PANEL - Kit Carton - 1000 IU

One single-use vial with 4 mL pre-filled diluent syringe
NDC 58394-014-01

1000 IU RANGE

xyntha®

Antihemophilic Factor
(Recombinant)

For Intravenous Administration.

For Factor VIII
Replacement
Therapy Only

Rx only

Pfizer

PRINCIPAL DISPLAY PANEL - 2000 IU Vial Label

2000 IU RANGE

xyntha®
Antihemophilic Factor
(Recombinant)

No Preservatives. Single Use.

NDC 58394-115-01

Manufactured by
Wyeth Pharmaceuticals LLC
A subsidiary of Pfizer Inc.
Philadelphia, PA 19101
US Govt. License No. 3

Pfizer

Rx only

For Factor VIII
Replacement

PRINCIPAL DISPLAY PANEL - Kit Carton - 2000 IU

One single-use vial with 4 mL pre-filled diluent syringe
NDC 58394-015-01

2000 IU RANGE

xyntha®

Antihemophilic Factor
(Recombinant)

For Intravenous Administration.

For Factor VIII
Replacement
Therapy Only

Rx only

Pfizer